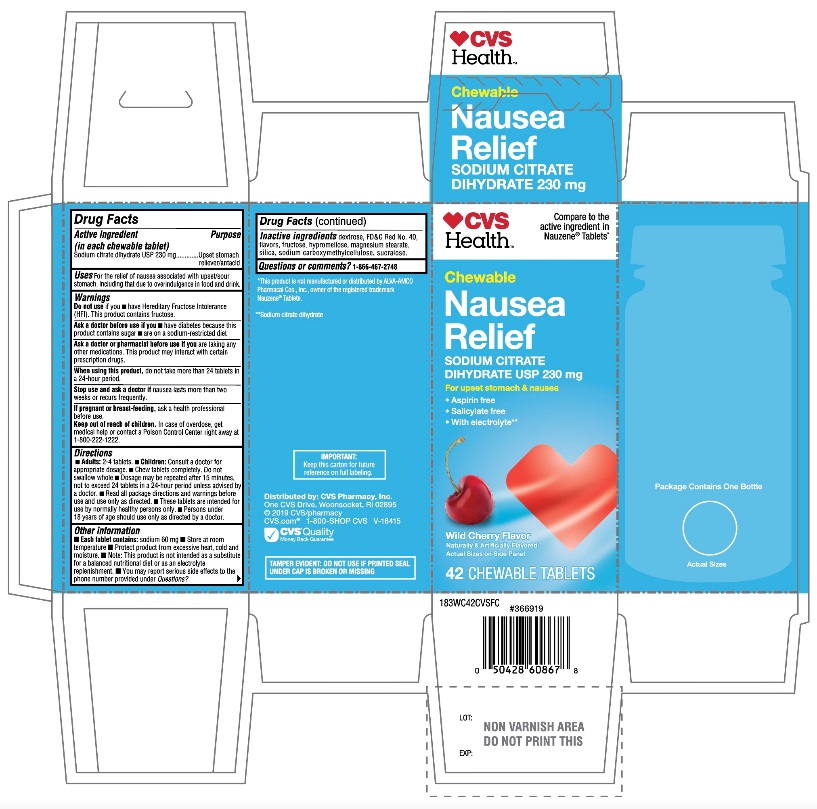 DRUG LABEL: CVS Health

NDC: 69842-423 | Form: TABLET, CHEWABLE
Manufacturer: CVS PHARMACY,INC.
Category: otc | Type: HUMAN OTC DRUG LABEL
Date: 20251208

ACTIVE INGREDIENTS: TRISODIUM CITRATE DIHYDRATE 230 mg/1 1
INACTIVE INGREDIENTS: DEXTROSE, UNSPECIFIED FORM; FD&C RED NO. 40; CHERRY; FRUCTOSE; HYPROMELLOSE, UNSPECIFIED; MAGNESIUM STEARATE; SILICON DIOXIDE; CARBOXYMETHYLCELLULOSE SODIUM, UNSPECIFIED; SUCRALOSE

CVS Health Chewable Nausea Relief

Active ingredient (in each chewable tablet)

Sodium citrate dehydrate USP 230 mg

Purpose

Upset stomach reliever/antacid

Uses

For the relief of nausea associated with upset/sour stomach, including that due to overindulgence in food and drink.

DO NOT USE

Do not useif you have Hereditary Fructose Intolerance (HFI). This product contains fructose.

Ask a doctor before use if you

- have diabetes because this product contains sugar
- are on a sodium-restricted diet

Ask a doctor or pharmacist before use if you aretaking any other medications. This product may interact with certain prescription drugs.

When using this product,do not take more than 24 tablets in a 24-hour period.

Stop use and ask a doctor ifnausea lasts more than two weeks or recurs frequently.

PREGNANCY OR BREAST FEEDING

If pregnant or breastfeeding,ask a health professional before use.

Keep out of reach of children. In case of overdose, get medical help or contact a Poison Control Center right away at 1-800-222-1222.

Directions

- Adults: 2-4 tablets.
- Children: Consult a doctor for appropriate dosage.
- Chew tablets completely. Do not swallow tablet whole.
- Dosage may be repeated after 15 minutes, not to exceed 24 tablets in a 24-hour period unless advised by a doctor.
- Read all package directions and warning before use and use only as directed.
- These tablets are intended for use by normally healthy persons only.
- Persons under 18 years of age should use only as directed by a doctor.

Other information

- Each tablet contains:sodium 60 mg
- Store at room temperature.
- Protect product from excessive heat, cold and moisture.
- Note: This product is not intended as a substitute for a balanced nutritional diet or as an electrolyte replenishment.
- You may report serious side effects to the phone number provided under Questions?

Inactive ingredients

dextrose, FDC Red No. 40, flavors, fructose, hypromellose, magnesium stearate, silica, sodium carboxymethylcellulose, sucralose.

Questions

1-866-467-2748

Principal Display Panel

CVS Health™

Compare to the active ingredient in Nauzene® Tablets*

NDC# 69842-423-42

Chewable

Nausea Relief

SODIUM CITRATE

DIHYDRATE USP 230 mg

For upset stomach & nausea

- Aspirin free
- Salicylate free
- With electrolyte**

Wild Cherry Flavor

Naturally & Artificially Flavored

42 CHEWABLE TABLETS

TAMPER EVIDENT: DO NOT USE IF PRINTED SEAL UNDER CAP IS BROKEN OR MISSING

IMPORTANT: Keep this carton for future reference on full labeling

Distributed by: CVS Pharmacy, Inc.

One CVS Drive, Woonsocket, RI 02895

© 2019 CVS/pharmacy

CVS.com® 1-800-SHOP CVS V-16415

CVS® Quality

Money Back Guarantee

*This product is not manufactured of distributed by ALVA-AMCO Pharmacal Cos., Inc., the distributor of Nauzene® Tablets.

**Sodium citrate dehydrate